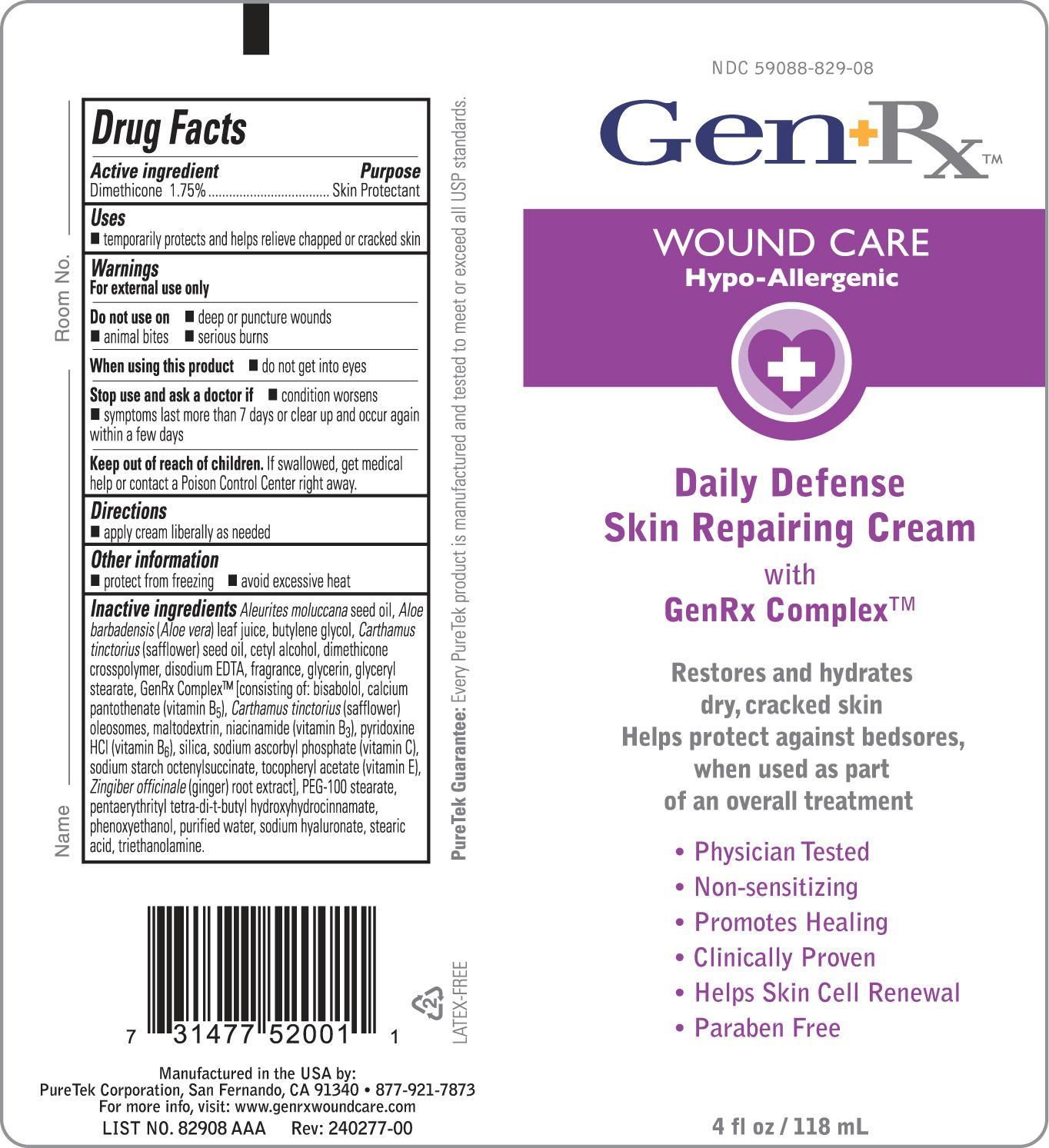 DRUG LABEL: GenRx Daily Defense Skin Repairing
NDC: 59088-829 | Form: CREAM
Manufacturer: PureTek Corporation
Category: otc | Type: HUMAN OTC DRUG LABEL
Date: 20241016

ACTIVE INGREDIENTS: DIMETHICONE 17.5 mg/1 mL
INACTIVE INGREDIENTS: KUKUI NUT OIL; ALOE VERA LEAF; BUTYLENE GLYCOL; SAFFLOWER OIL; CETYL ALCOHOL; DIMETHICONE/DIENE DIMETHICONE CROSSPOLYMER; EDETATE DISODIUM; GLYCERIN; GLYCERYL MONOSTEARATE; LEVOMENOL; CALCIUM PANTOTHENATE; CARTHAMUS TINCTORIUS SEED OLEOSOMES; MALTODEXTRIN; NIACINAMIDE; PYRIDOXINE HYDROCHLORIDE; SILICON DIOXIDE; SODIUM ASCORBYL PHOSPHATE; .ALPHA.-TOCOPHEROL ACETATE, DL-; GINGER; PEG-100 STEARATE; PENTAERYTHRITOL TETRAKIS(3-(3,5-DI-TERT-BUTYL-4-HYDROXYPHENYL)PROPIONATE); PHENOXYETHANOL; WATER; HYALURONATE SODIUM; STEARIC ACID; TROLAMINE

GenRx Daily Defense Skin Repairing

Active ingredient

Dimethicone 1.75%

Purpose

Skin Protectant

Uses

■ temporarily protects and helps relieve chapped or cracked skin

Warnings

For external use only

Do not use on

■ deep or puncture wounds ■ animal bites ■ serious burns

When using this product

■ do not get into eyes

Stop use and ask a doctor if

■ condition worsens
■ symptoms last more than 7 days or clear up and occur again within a few days

Keep out of reach of children.

If swallowed, get medical help or contact a Poison Control Center right away.

Directions

■ apply cream liberally as needed

Other information

■ protect from freezing ■ avoid excessive heat

Inactive ingredients

Aleurites moluccanaseed oil, Aloe barbadensis(Aloe vera) leaf juice, butylene glycol, Carthamus tinctorius(safflower) seed oil, cetyl alcohol, dimethicone crosspolymer, disodium EDTA, fragrance, glycerin, glyceryl stearate, GenRx Complex™ [consisting of: bisabolol, calcium pantothenate (vitamin B5), Carthamus tinctorius(safflower) oleosomes, maltodextrin, niacinamide (vitamin B3), pyridoxine HCl (vitamin B6), silica, sodium ascorbyl phosphate (vitamin C), sodium starch octenylsuccinate, tocopheryl acetate (vitamin E), Zingiber officinale(ginger) root extract], PEG-100 stearate, pentaerythrityl tetra-di-t-butyl hydroxyhydrocinnamate, phenoxyethanol, purified water, sodium hyaluronate, stearic acid, triethanolamine.